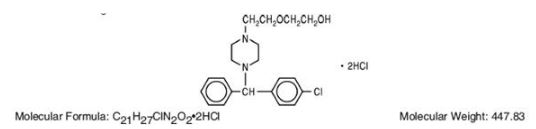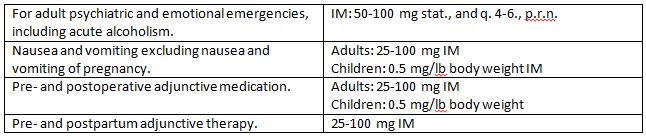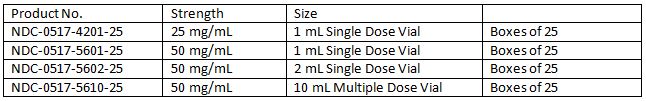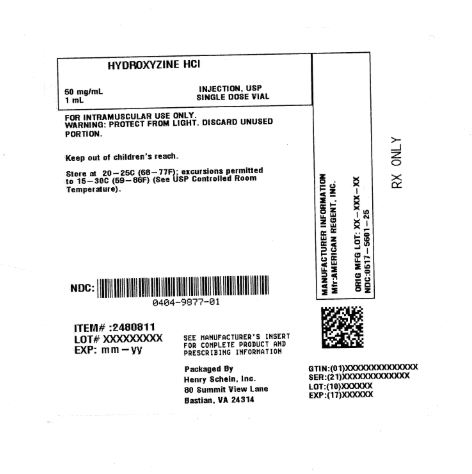 DRUG LABEL: Hydroxyzine Hydrochloride
NDC: 0404-9877 | Form: INJECTION, SOLUTION
Manufacturer: Henry Schein, Inc.
Category: prescription | Type: HUMAN PRESCRIPTION DRUG LABEL
Date: 20251031

ACTIVE INGREDIENTS: HYDROXYZINE DIHYDROCHLORIDE 50 mg/1 mL
INACTIVE INGREDIENTS: HYDROCHLORIC ACID; SODIUM HYDROXIDE

Hydroxyzine HCL 50 mg/mL Injection, USP 1mL Single Dose Vial

Description

Hydroxyzine hydrochloride has the chemical name of (±)-2-[2-[4-(p-Chloro-a phenylbenzyl) -1-piperazinyl]ethoxy]ethanol dihydrochloride and occurs as a white, odorless powder which is very soluble in water.

It has the following structural formula:

Molecular Formula: C21H27CIN202•2HCI Molecular Weight: 447.83

Hydroxyzine Hydrochloride Injection, USP is a sterile aqueous solution intended for intramuscular administration.

Each mL contains: Hydroxyzine HCI 25 mg or 50 mg, Benzyl Alcohol 0.9%, and Water for Injection q.s. pH adjusted with Sodium Hydroxide and/or Hydrochloric Acid.

Clinical Pharmacology

Hydroxyzine hydrochloride is unrelated chemically to phenothiazine, reserpine, and meprobamate. Hydroxyzine has demonstrated its clinical effectiveness in the chemotherapeutic aspect of the total management of neuroses and emotional disturbances manifested by anxiety, tension, agitation, apprehension or confusion.

Hydroxyzine has been shown clinically to be a rapid-acting true ataraxic with a wide margin of safety. It induces a calming effect in anxious, tense, psychoneurotic adults and also in anxious, hyperkinetic children without impairing mental alertness. It is not a cortical depressant, but its action may be due to a suppression of activity in certain key regions of the subcortical area of the central nervous system.

Primary skeletal muscle relaxation has been demonstrated experimentally.

Hydroxyzine has been shown experimentally to have antispasmodic properties, apparently mediated through interference with the mechanism that responds to spasmogenic agents such as serotonin, acetylcholine, and histamine.

Antihistaminic effects have been demonstrated experimentally and confirmed clinically.

An antiemetic effect, both by the apomorphine test and the veriloid test, has been demonstrated. Pharmacological and clinical studies indicate that hydroxyzine in therapeutic dosage does not increase gastric secretion or acidity and in most cases provides mild antisecretory benefits.

Indications and Usage

The total management of anxiety, tension, and psychomotor agitation in conditions of emotional stress requires in most instances a combined approach of psychotherapy and chemotherapy. Hydroxyzine has been found to be particularly useful for this latter phase of therapy in its ability to render the disturbed patient more amenable to psychotherapy in long term treatment of the psychoneurotic and psychotic, although it should not be used as the sole treatment of psychosis or of clearly demonstrated cases of depression.

Hydroxyzine is also useful in alleviating the manifestations of anxiety and tension as in the preparation for dental procedures and in acute emotional problems. It has also been recommended for the management of anxiety associated with organic disturbances and as adjunctive therapy in alcoholism and allergic conditions with strong emotional overlay, such as in asthma, chronic urticaria, and pruritus.

Hydroxyzine hydrochloride intramuscular solution is useful in treating the following types of patients when intramuscular administration is indicated:

1. The acutely disturbed or hysterical patient.

2. The acute or chronic alcoholic with anxiety withdrawal symptoms or delirium tremens.

3. As pre- and postoperative and pre- and postpartum adjunctive medication to permit reduction in narcotic dosage, allay anxiety and control emesis.

Hydroxyzine hydrochloride has also demonstrated effectiveness in controlling nausea and vomiting, excluding nausea and vomiting of pregnancy. (See CONTRAINDICATIONS).

In prepartum states, the reduction in narcotic requirement effected by hydroxyzine is of particular benefit to both mother and neonate.

Hydroxyzine benefits the cardiac patient by its ability to allay the associated anxiety and apprehension attendant to certain types of heart disease. Hydroxyzine is not known to interfere with the action of digitalis in any way and may be used concurrently with this agent.

The effectiveness of hydroxyzine in long term use, that is, more than 4 months, has not been assessed by systematic clinical studies. The physician should reassess periodically the usefulness of the drug for the individual patient.

Contraindications

Hydroxyzine hydrochloride intramuscular solution is intended only for intramuscular administration and should not, under any circumstances, be injected subcutaneously, intra arterially or intravenously.

Hydroxyzine is contraindicated in patients with a prolonged QT interval.

This drug is contraindicated for patients who have shown a previous hypersensitivity to it.

Hydroxyzine, when administered to the pregnant mouse, rat, and rabbit, induced fetal abnormalities in the rat at doses substantially above the human therapeutic range. Clinical data in human beings are inadequate to establish safety in early pregnancy. Until such data are available, hydroxyzine is contraindicated in early pregnancy.

Warnings

Tissue damage: Intramuscular hydroxyzine hydrochloride may result in severe injection site reactions (including extensive tissue damage, necrosis and gangrene) requiring surgical intervention (including debridement, skin grafting and amputation).

Adverse Reactions

Therapeutic doses of hydroxyzine seldom produce impairment of mental alertness. However, drowsiness may occur; if so, it is usually transitory and may disappear in a few days of continued therapy or upon reduction of the dose. Dryness of the mouth may be encountered at higher doses. Extensive clinical use has substantiated the absence of toxic effects on the liver or bone marrow when administered in the recommended doses for over four years of uninterrupted therapy. The absence of adverse effects has been further demonstrated in experimental studies in which excessively high doses were administered.

Involuntary motor activity, including rare instances of tremor and convulsions, has been reported, usually with doses considerably higher than those recommended. Continuous therapy with over one gram per day has been employed in some patients without these effects having been encountered. Hydroxyzine hydrochloride is associated with Acute Generalized Exanthematous Pustulosis (AGEP) in post marketing reports.

Dosage and Administration

The recommended dosages for hydroxyzine hydrochloride intramuscular solution are:

As with all potent medications, the dosage should be adjusted according to the patient's response to therapy.

FOR ADDITIONAL INFORMATION ON THE ADMINISTRATION AND SITE OF SELECTION SEE PRECAUTIONS SECTION. NOTE: Hydroxyzine hydrochloride intramuscular solution may be administered without further dilution.

Patients may be started on intramuscular therapy when indicated. They should be maintained on oral therapy whenever this route is practicable.

Parenteral drug products should be inspected visually for particulate matter and discoloration prior to administration, whenever solution and container permit.

How Supplied

Storage Condition: Store at 20° to 25°C (68° to 7JOF); excursions permitted to 15° to 30°C (59° to 86°F) (See USP Controlled Room Temperature). Protect from light. Discard unused portion of the single dose vial.

Product repackaged by: Henry Schein, Inc., Bastian, VA 24314
From Original Manufacturer/Distributor's NDC and Unit of Sale | To Henry Schein Repackaged Product NDC and Unit of Sale | Total Strength/Total Volume (Concentration) per unit
NDC 0517-5601-25 Boxes of 25 | NDC 0404-9877-01 1 1mL Single Dose Vial in a bag (Vial bears NDC 0517-5601-25) | 50 mg/mL
NDC 0517-5602-25 Boxes of 25 | NDC 0404-9878-02 1 2 mL Single Dose Vial in a bag (Vial bears NDC 0517-5602-25) | 50 mg/mL

AMERICAN REGENT, INC.

SHIRLEY, NY 11967

IN4201

Rev. 10/16

MG #7842